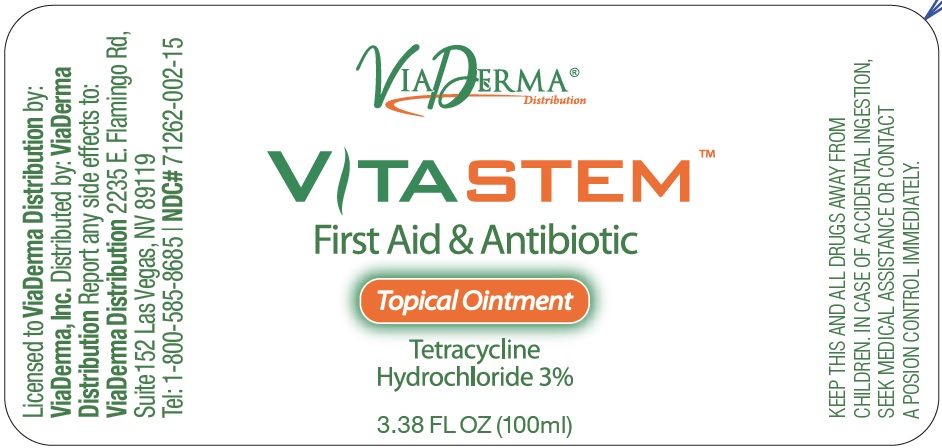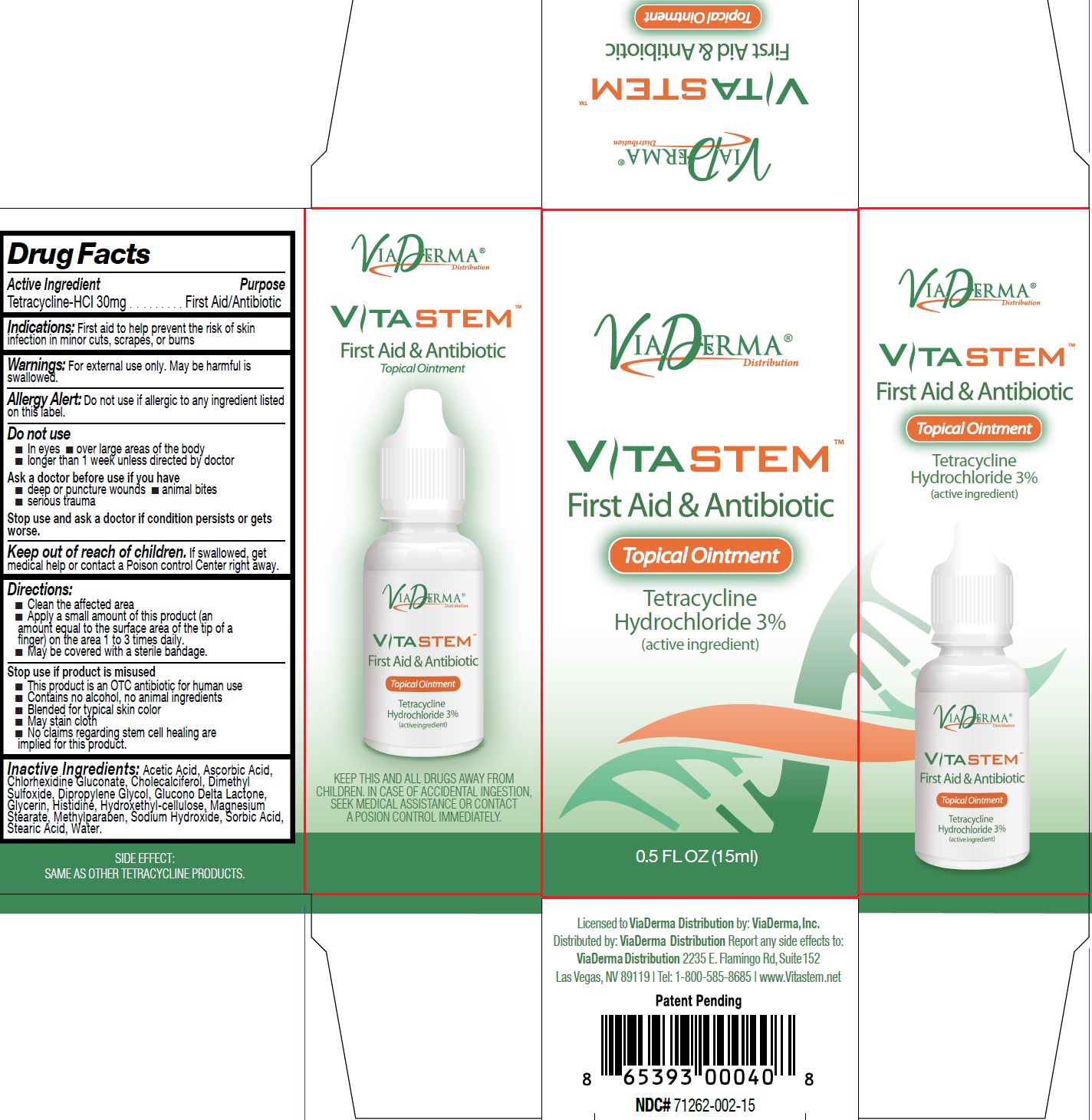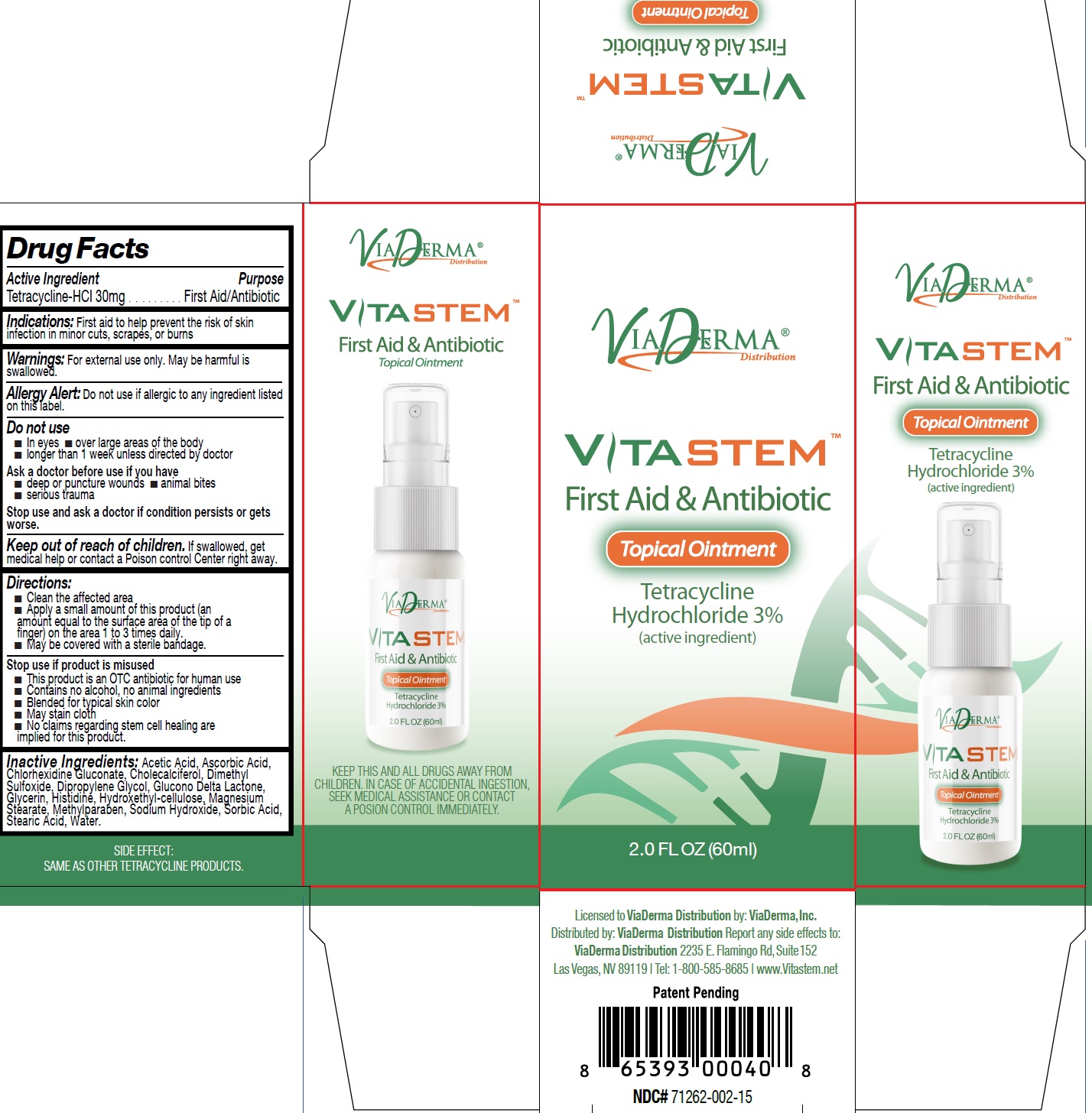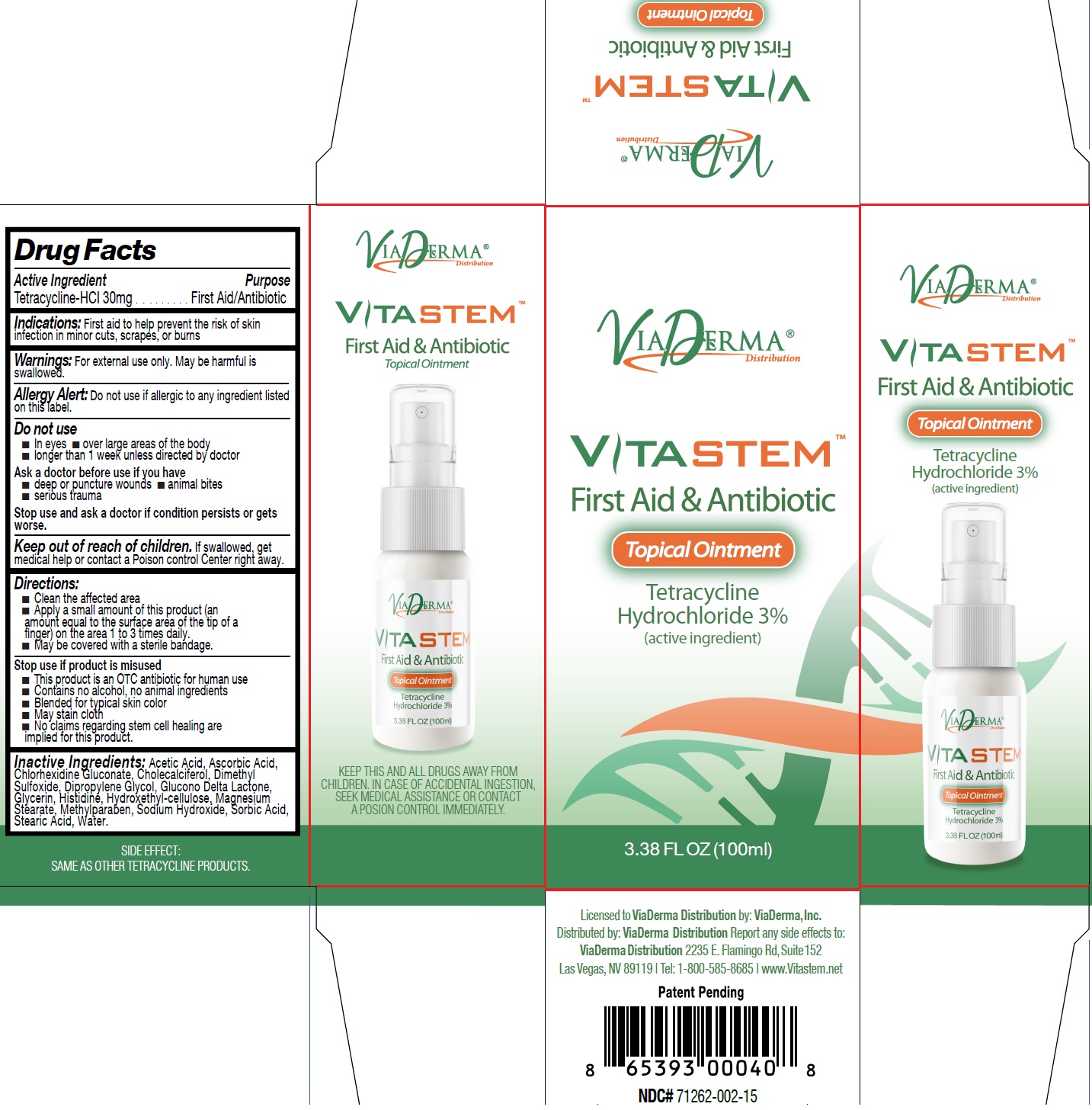 DRUG LABEL: Vitastem
NDC: 71262-002 | Form: OINTMENT
Manufacturer: ViaDerma Distribution, Inc.
Category: otc | Type: HUMAN OTC DRUG LABEL
Date: 20250218

ACTIVE INGREDIENTS: TETRACYCLINE HYDROCHLORIDE 30 mg/1 mL
INACTIVE INGREDIENTS: ACETIC ACID; ASCORBIC ACID; CHLORHEXIDINE GLUCONATE; CHOLECALCIFEROL; DIMETHYL SULFOXIDE; DIPROPYLENE GLYCOL; GLUCONOLACTONE; GLYCERIN; HISTIDINE; MAGNESIUM STEARATE; METHYLPARABEN; SODIUM HYDROXIDE; SORBIC ACID; STEARIC ACID; WATER

Vitastem

Active Ingredient

Tetracycline-HCI 30mg

Purpose

First Aid/Antibiotic

Indications:

First aid to help prevent the risk of skin infection in minor cuts, scrapes, or burns

Warnings:

For external use only. May be harmful is swallowed.

Do not use if allergic to any ingredient listed on this label. Allergy Alert:

Do not use

- In eyes
- over large areas of the body
- longer than 1 week unless directed by doctor

Ask a doctor before use if you have

- deep or puncture wounds
- animal bites
- serious trauma

Stop use and ask a doctor

if condition persists or gets worse.

Keep out of reach of children.

If swallowed, get medical help or contact a Poison control Center right away.

Directions:

- Clean the affected area
- Apply a small amount of this product (an amount equal to the surface area of the tip of a finger) on the area 1 to 3 times daily.
- May be covered with a sterile bandage.

- This product is an OTC antibiotic for human use
- Contains no alcohol, no animal ingredients
- Blended for typical skin color
- May stain cloth
- No claims regarding stem cell healing are implied for this product.

Stop use if product is misused

Inactive Ingredients:

Acetic Acid, Ascorbic Acid, Chlorhexidine Gluconate, Cholecalciferol, Dimethyl Sulfoxide, Dipropylene Glycol, Glucono Delta Lactone, Glycerin, Histidine, Hydroxethyl-cellulose, Magnesium Stearate, Methylparaben, Sodium Hydroxide, Sorbic Acid, Stearic Acid, Water.